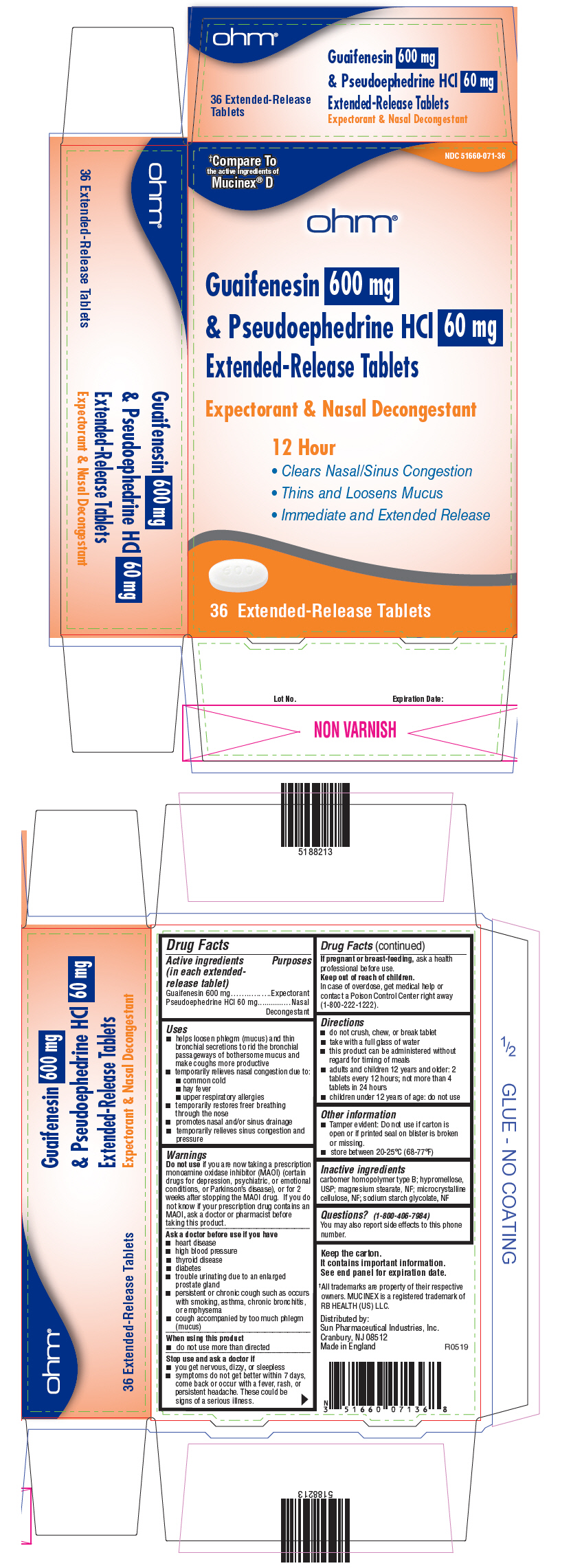 DRUG LABEL: Guaifenesin and Pseudoephedrine Hydrochloride
NDC: 51660-071 | Form: TABLET, EXTENDED RELEASE
Manufacturer: OHM LABORATORIES INC
Category: otc | Type: HUMAN OTC DRUG LABEL
Date: 20190621

ACTIVE INGREDIENTS: Guaifenesin 600 mg/1 1; Pseudoephedrine Hydrochloride 60 mg/1 1
INACTIVE INGREDIENTS: CARBOMER HOMOPOLYMER TYPE B (ALLYL PENTAERYTHRITOL CROSSLINKED); HYPROMELLOSE, UNSPECIFIED; MAGNESIUM STEARATE; MICROCRYSTALLINE CELLULOSE; SODIUM STARCH GLYCOLATE TYPE A POTATO

Guaifenesin and Pseudoephedrine Hydrochloride

Drug Facts

ACTIVE INGREDIENT

PURPOSE

Active ingredients (in each extended-release tablet) | Purposes
Guaifenesin 600 mg | Expectorant
Pseudoephedrine HCl 60 mg | Nasal Decongestant

Uses

- helps loosen phlegm (mucus) and thin bronchial secretions to rid the bronchial passageways of bothersome mucus and make coughs more productive
- temporarily relieves nasal congestion due to:
  - common cold
  - hay fever
  - upper respiratory allergies
- temporarily restores freer breathing through the nose
- promotes nasal and/or sinus drainage
- temporarily relieves sinus congestion and pressure

Warnings

Do not use if you are now taking a prescription monoamine oxidase inhibitor (MAOI) (certain drugs for depression, psychiatric, or emotional conditions, or Parkinson's disease), or for 2 weeks after stopping the MAOI drug. If you do not know if your prescription drug contains an MAOI, ask a doctor or pharmacist before taking this product.

Ask a doctor before use if you have

- heart disease
- high blood pressure
- thyroid disease
- diabetes
- trouble urinating due to an enlarged prostate gland
- persistent or chronic cough such as occurs with smoking, asthma, chronic bronchitis, or emphysema
- cough accompanied by too much phlegm (mucus)

When using this product

- do not use more than directed

Stop use and ask a doctor if

- you get nervous, dizzy, or sleepless
- symptoms do not get better within 7 days, come back or occur with a fever, rash, or persistent headache. These could be signs of a serious illness.

PREGNANCY OR BREAST FEEDING

If pregnant or breast-feeding, ask a health professional before use.

Keep out of reach of children.

In case of overdose, get medical help or contact a Poison Control Center right away (1-800-222-1222).

Directions

- do not crush, chew, or break tablet
- take with a full glass of water
- this product can be administered without regard for timing of meals
- adults and children 12 years and older: 2 tablets every 12 hours; not more than 4 tablets in 24 hours
- children under 12 years of age: do not use

Other information

- Tamper evident: Do not use if carton is open or if printed seal on blister is broken or missing.
- store between 20-25°C (68-77°F)

Inactive ingredients

carbomer homopolymer type B; hypromellose, USP; magnesium stearate, NF; microcrystalline cellulose, NF; sodium starch glycolate, NF

Questions?

(1-800-406-7984)

You may also report side effects to this phone number.

Distributed by:
Sun Pharmaceutical Industries, Inc.
Cranbury, NJ 08512

PRINCIPAL DISPLAY PANEL - 600 mg/60 mg Tablet Blister Pack Carton

†Compare To
the active ingredients of
Mucinex® D

NDC 51660-071-36

ohm®

Guaifenesin 600 mg
& Pseudoephedrine HCl 60 mg
Extended-Release Tablets

Expectorant & Nasal Decongestant

12 Hour

- Clears Nasal/Sinus Congestion
- Thins and Loosens Mucus
- Immediate and Extended Release

36 Extended-Release Tablets